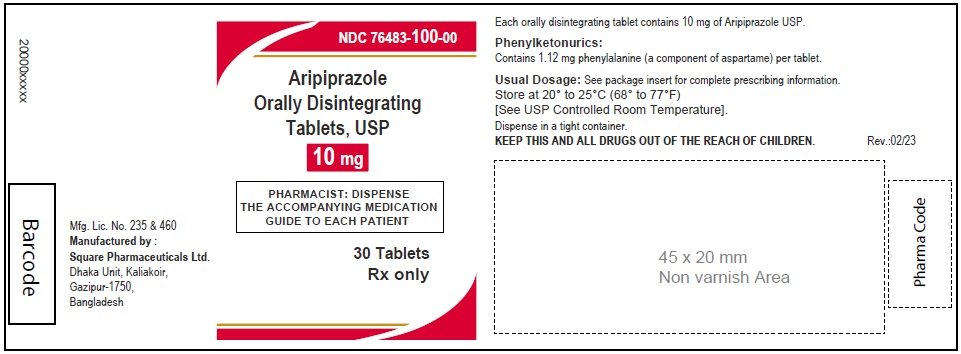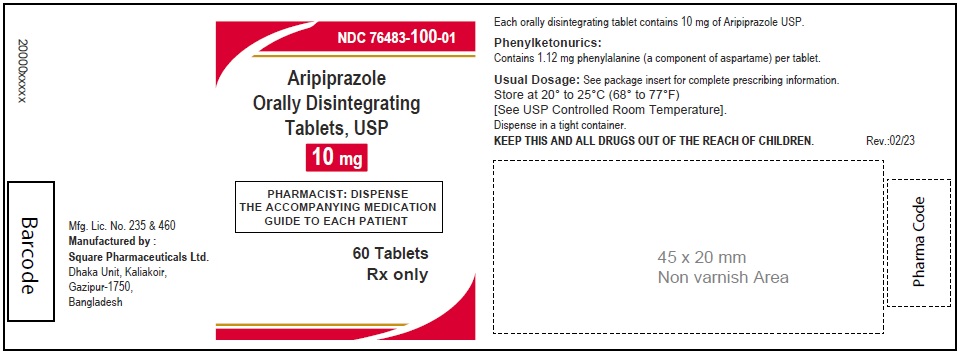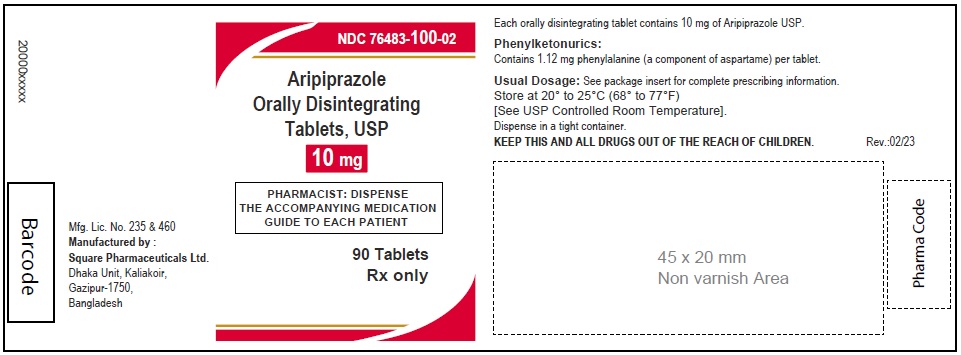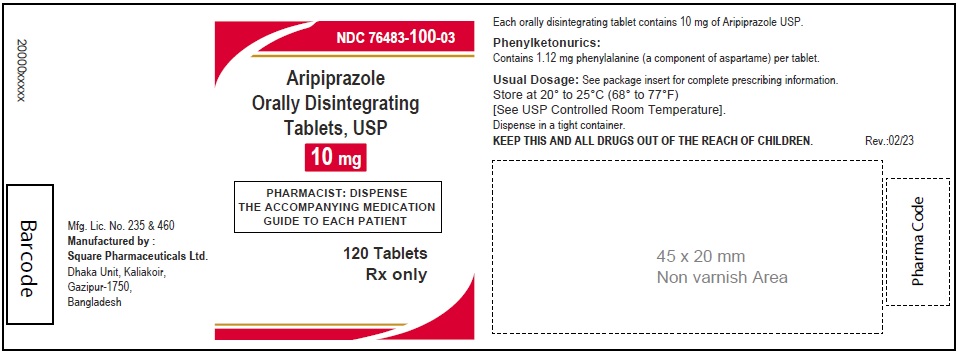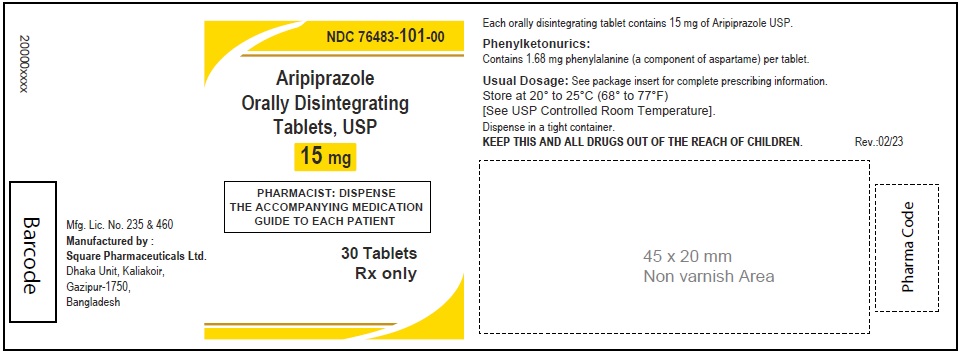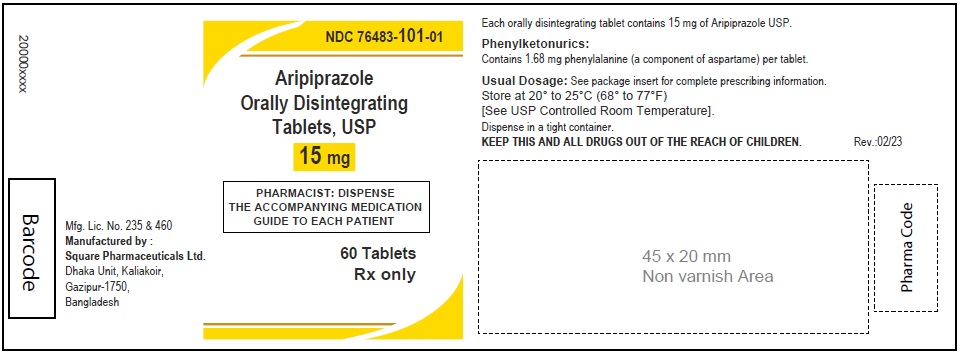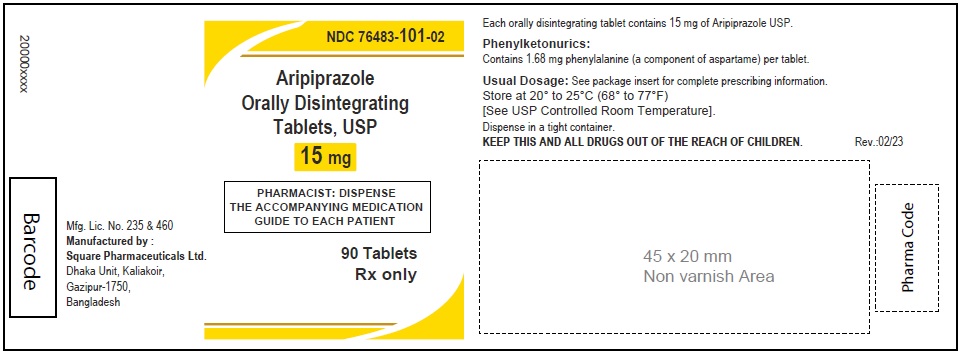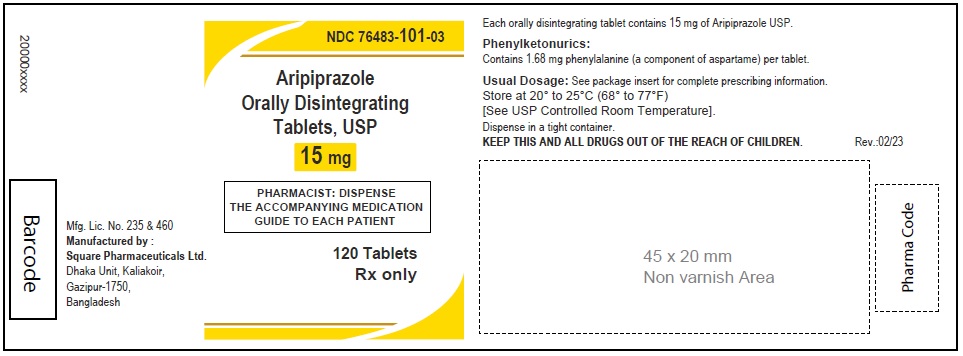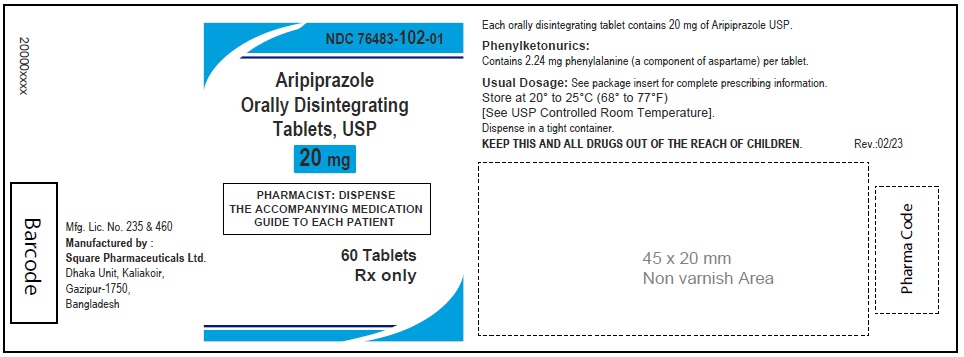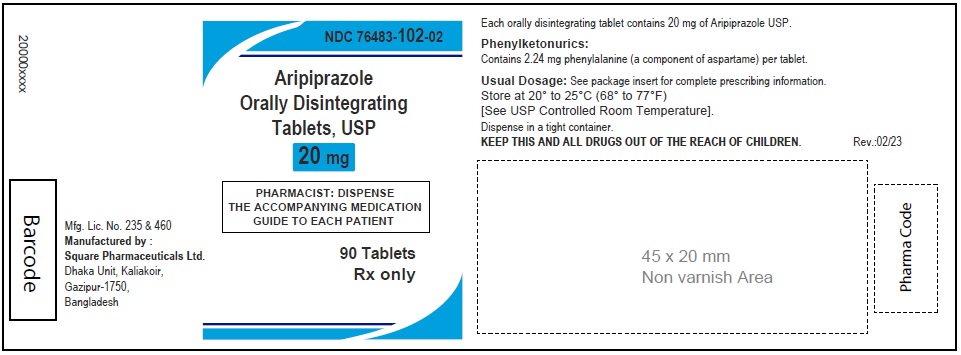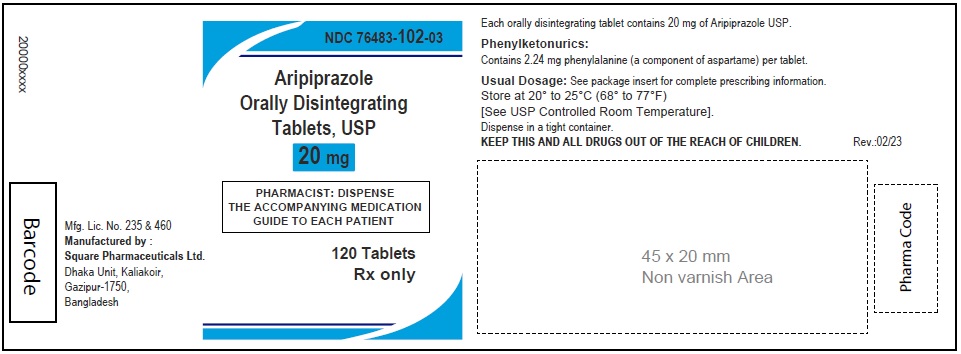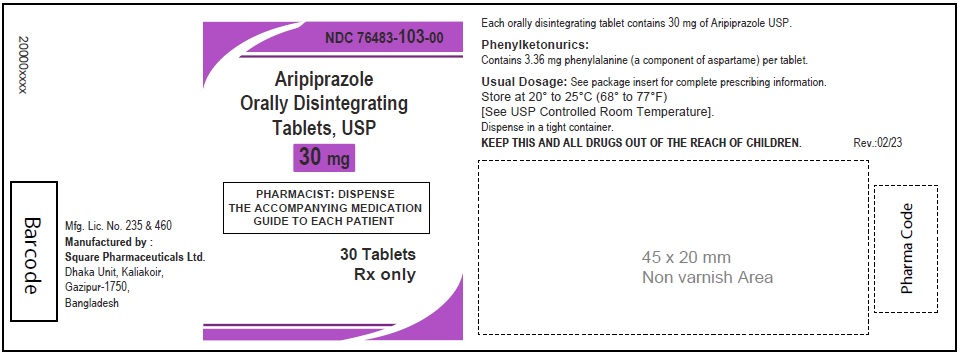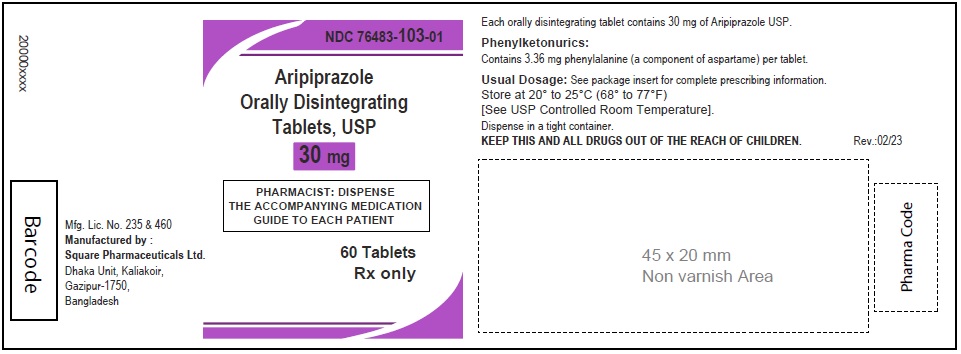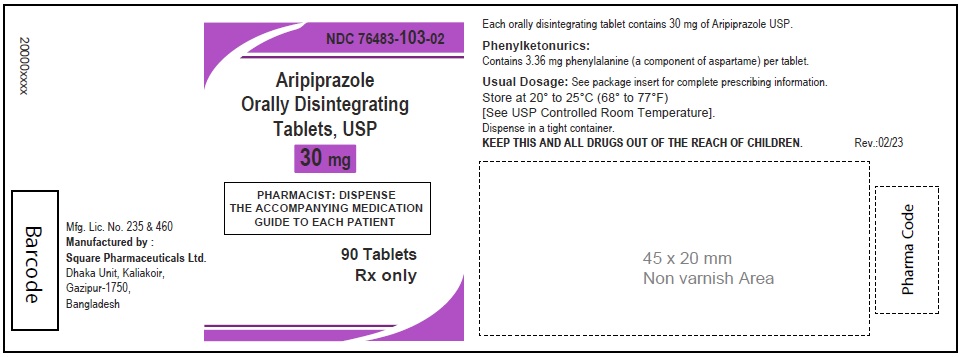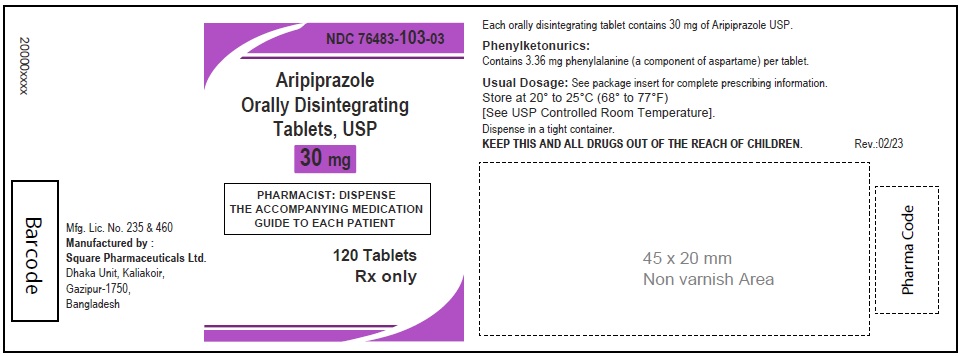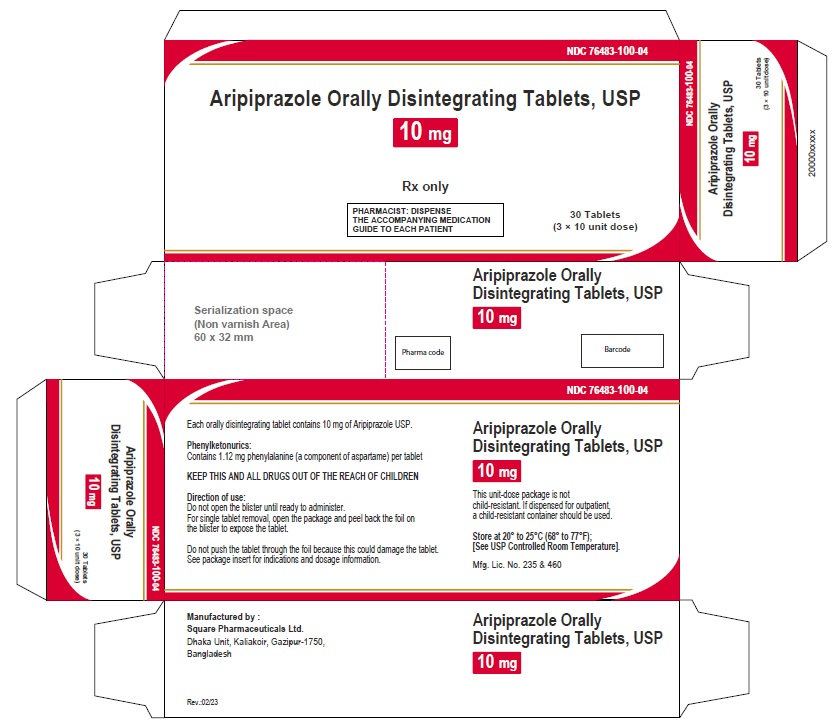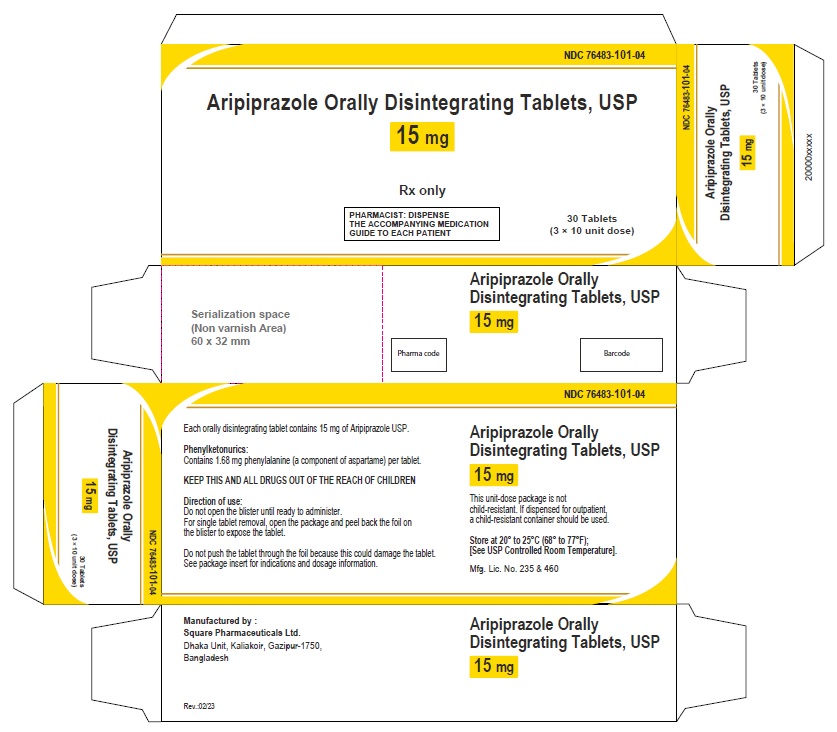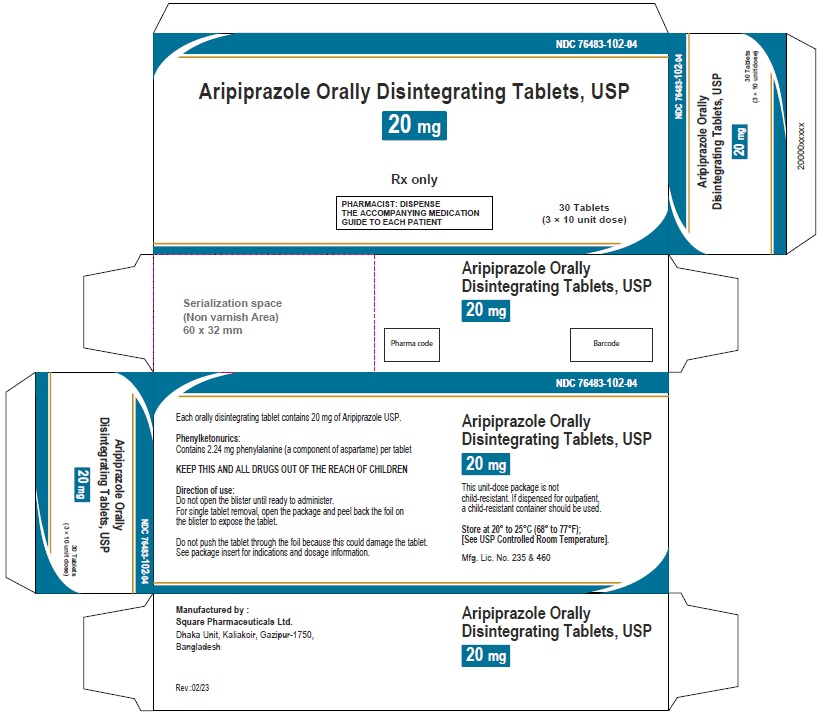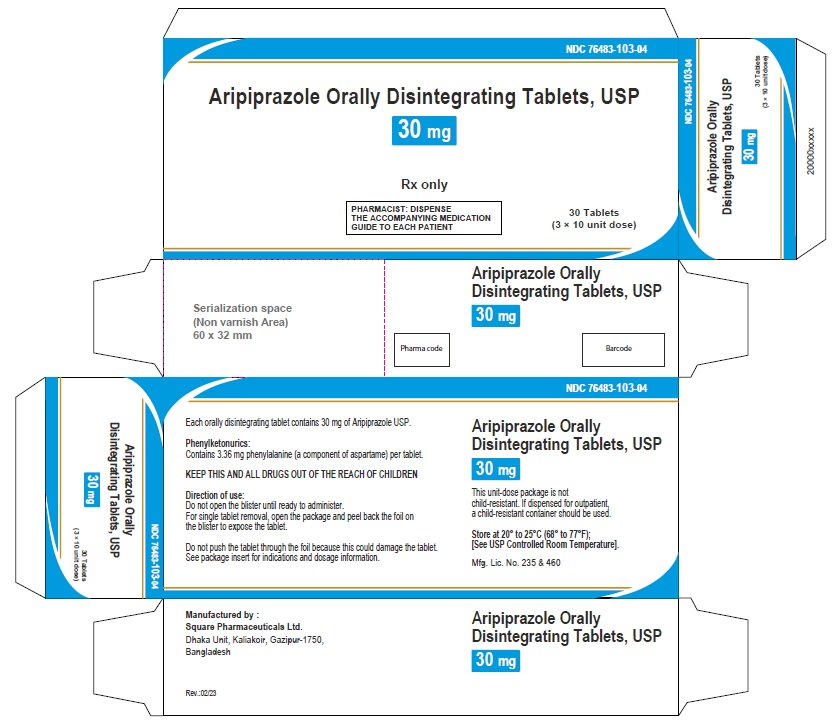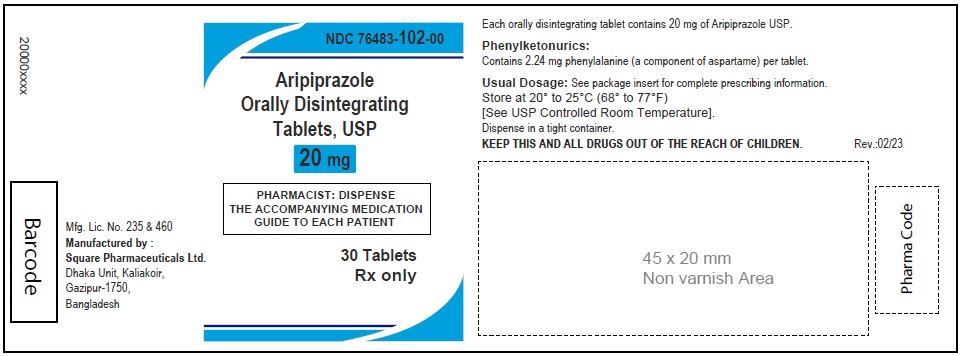 DRUG LABEL: Aripiprazole
NDC: 76483-100 | Form: TABLET, ORALLY DISINTEGRATING
Manufacturer: SQUARE PHARMACEUTICALS LIMITED
Category: prescription | Type: HUMAN PRESCRIPTION DRUG LABEL
Date: 20230702

ACTIVE INGREDIENTS: ARIPIPRAZOLE 10 mg/1 1
INACTIVE INGREDIENTS: ASPARTAME; CALCIUM STEARATE; CROSPOVIDONE; PEPPERMINT; MANNITOL

ARIPIPRAZOLE ORALLY DISINTEGRATING TABLETS

PACKAGE LABEL.PRINCIPAL DISPLAY PANEL

NDC 76483-100-00

Aripiprazole Orally Disintegrating Tablets, USP 10 mg

30 Tablets

Rx Only

NDC 76483-100-01

Aripiprazole Orally Disintegrating Tablets, USP 10 mg

60 Tablets

Rx Only

NDC 76483-100-02

Aripiprazole Orally Disintegrating Tablets, USP 10 mg

90 Tablets

Rx Only

NDC 76483-100-03

Aripiprazole Orally Disintegrating Tablets, USP 10 mg

120 Tablets

Rx Only

NDC 76483-101-00

Aripiprazole Orally Disintegrating Tablets, USP 15 mg

30 Tablets

Rx Only

NDC 76483-101-01

Aripiprazole Orally Disintegrating Tablets, USP 15 mg

60 Tablets

Rx Only

NDC 76483-101-02

Aripiprazole Orally Disintegrating Tablets, USP 15 mg

90 Tablets

Rx Only

NDC 76483-101-03

Aripiprazole Orally Disintegrating Tablets, USP 15 mg

120 Tablets

Rx Only

NDC 76483-102-00

Aripiprazole Orally Disintegrating Tablets, USP 20 mg

30 Tablets

Rx Only

NDC 76483-102-01

Aripiprazole Orally Disintegrating Tablets, USP 20 mg

60 Tablets

Rx Only

NDC 76483-102-02

Aripiprazole Orally Disintegrating Tablets, USP 20 mg

90 Tablets

Rx Only

NDC 76483-102-03

Aripiprazole Orally Disintegrating Tablets, USP 20 mg

120 Tablets

Rx Only

NDC 76483-103-00

Aripiprazole Orally Disintegrating Tablets, USP 30 mg

30 Tablets

Rx Only

NDC 76483-103-01

Aripiprazole Orally Disintegrating Tablets, USP 30 mg

60 Tablets

Rx Only

NDC 76483-103-02

Aripiprazole Orally Disintegrating Tablets, USP 30 mg

90 Tablets

Rx Only

NDC 76483-103-03

Aripiprazole Orally Disintegrating Tablets, USP 30 mg

120 Tablets

Rx Only

Aripiprazole Orally Disintegrating Tablets 10 mg (30 Tablets in 1 Carton)

Each orally disintegrating tablet contains 10 mg aripiprazole USP

NDC 76483-100-04

Rx Only

Aripiprazole Orally Disintegrating Tablets 15 mg (30 Tablets in 1 Carton)

Each orally disintegrating tablet contains 15 mg aripiprazole USP

NDC 76483-101-04

Rx Only

Aripiprazole Orally Disintegrating Tablets, 20 mg (30 Tablets in 1 Carton)

Each orally disintegrating tablet contains 20 mg aripiprazole USP

NDC 76483-102-04

Rx Only

Aripiprazole Orally Disintegrating Tablets 30 mg (30 Tablets in 1 Carton)

Each orally disintegrating tablet contains 30 mg aripiprazole USP

NDC 76483-103-04

Rx Only